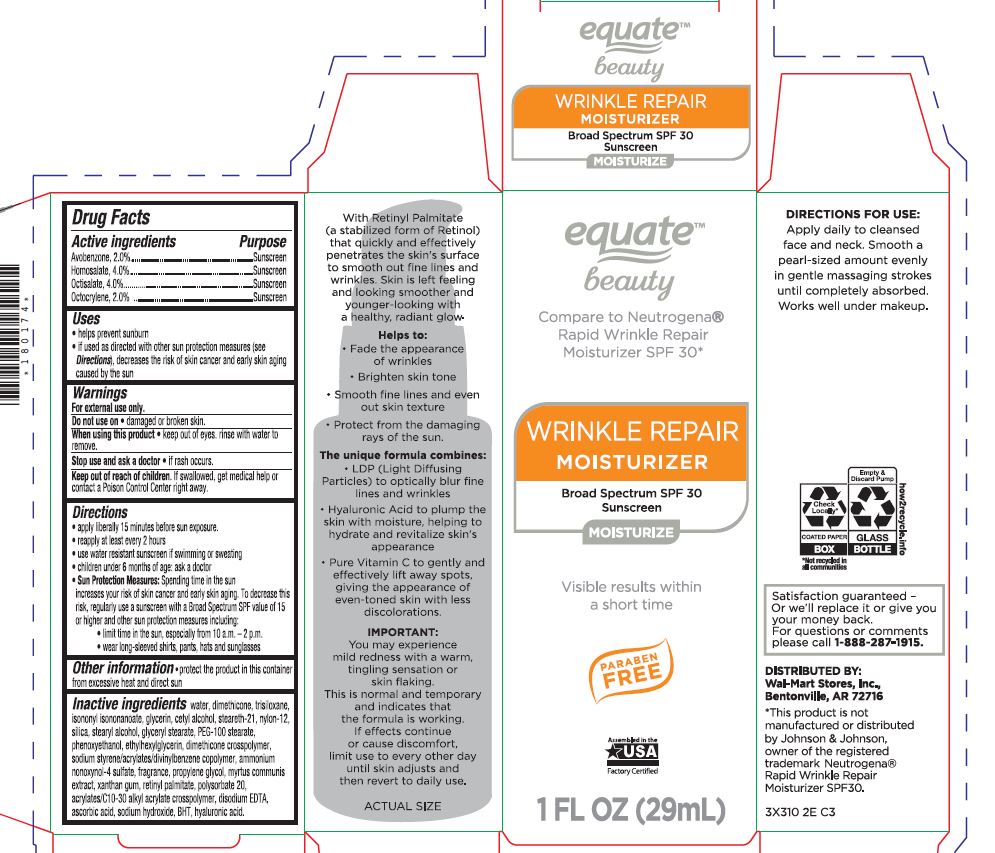 DRUG LABEL: Wrinkle Repair Moisturizer SPF 30
NDC: 79903-205 | Form: LOTION
Manufacturer: Walmart
Category: otc | Type: HUMAN OTC DRUG LABEL
Date: 20260120

ACTIVE INGREDIENTS: AVOBENZONE 2 g/100 mL; HOMOSALATE 4 g/100 mL; OCTISALATE 4 g/100 mL; OCTOCRYLENE 2 g/100 mL
INACTIVE INGREDIENTS: WATER; TRISILOXANE; ISONONYL ISONONANOATE; GLYCERIN; STEARETH-21; NYLON-12; SILICON DIOXIDE; CETYL ALCOHOL; STEARYL ALCOHOL; GLYCERYL STEARATE SE; PEG-100 STEARATE; PHENOXYETHANOL; ETHYLHEXYLGLYCERIN; DIMETHICONE CROSSPOLYMER (450000 MPA.S AT 12% IN CYCLOPENTASILOXANE); STYRENE/ACRYLAMIDE COPOLYMER (500000 MW); MYRTUS COMMUNIS TOP; XANTHAN GUM; VITAMIN A PALMITATE; POLYSORBATE 20; EDETATE DISODIUM ANHYDROUS; ASCORBIC ACID; SODIUM HYDROXIDE; BUTYLATED HYDROXYTOLUENE; HYALURONIC ACID

PLSF-1831 Wrinkle Repair Moisturizer SPF 30

Active ingredients Purpose

Avonenzone 2% Sunscreen

Homosalate 4% Sunscreen

Octisalate 4% Sunscreen

Octocrylene 2% Sunscreen

Uses

•helps prevent sunburn• If used as directed with other sun protection measures (see Oirections),decreases the risk of skin cancer and early skin aging caused by the sun.

Do not use on

• damaged or broken skin.

When using this product

•keep out of eyes. Rinse with waterto remove.

Stop use and ask a doctor

• if rash occurs.

Directions:

• apply liberal 15 minutes before sun exposure• reapply at least every 2 hours •use a water resistant sunscreen if swimmingor sweating•children under 6 months of age: ask a doctor• Sun Protection Measures:Spending time in the sun increase your risk of skin cancer and early skin aging. To decrease this risk. regularly usea sunscreen wrtha Broad Spectrum SPF value of15 or higher and other suncrin protection measures including:
• limrt time in the sun, especial from 10a.m. -2 p.rn.•wear long-sleeve shorts , pants, hats and sunglasses